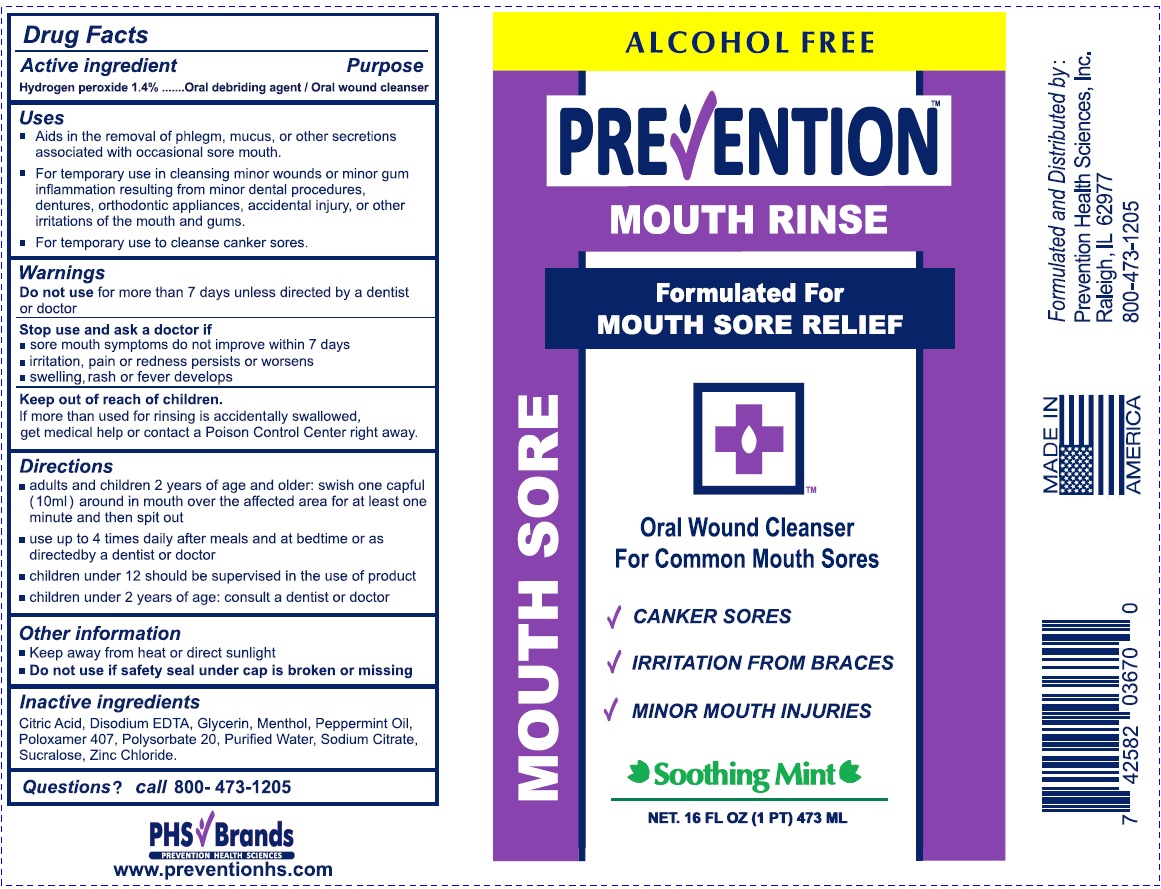 DRUG LABEL: Prevention Mouth Sore Rinse
NDC: 69951-004 | Form: LIQUID
Manufacturer: Prevention Health Sciences, Inc.
Category: otc | Type: HUMAN OTC DRUG LABEL
Date: 20250101

ACTIVE INGREDIENTS: HYDROGEN PEROXIDE 1.4 g/100 mL
INACTIVE INGREDIENTS: CITRIC ACID MONOHYDRATE; WATER; EDETATE DISODIUM; GLYCERIN; MENTHOL; PEPPERMINT OIL; POLOXAMER 407; SODIUM CITRATE; ZINC CHLORIDE; POLYSORBATE 20; SUCRALOSE

Prevention Mouth Sore Relief

Active ingredient

Hydrogen peroxide 1.4%

Purpose

Oral debriding agent / Oral wound cleanser

Uses

- Aids in the removal of phlegm, mucus or other secretions associated with occasional sore mouth.
- For temporary use in cleansing minor wounds or minor gum inflammation resulting from minor dental procedures, dentures, orthodontic appliances, accidental injury, or other irritations of the mouth and gums.
- For temporary use to cleanse canker sores.

Do not use for more than 7 days unless directed by a dentist or doctor

Stop use and ask a doctor if

- sore mouth symptoms do not improve within 7 days
- irritation, pain or redness persists or worsens
- swelling, rash or fever develops

Keep out of reach of children. If more than used for rinsing is accidentally swallowed, get medical help or contact a Poison Control Center right away.

Directions

- adults and children 2 years of age and older: swish one capful (10 ml) around in mouth over affected area for at least one minute and then spit out
- use up to 4 times daily after meals and at bedtime or as directed by a dentist or doctor
- children under 12 should be supervised in the use of product.
- children under 2 years of age: consult a dentist or doctor.

Other information

- keep away from heat or direct sunlight
- Do not use if safey seal under cap is broken or missing

INACTIVE INGREDIENT

Inactive ingredients Citric Acid, Disodium EDTA, Glycerin, Menthol, Peppermint Oil, Poloxamer 407, Polysorbate 20, Purified Water, Sodium Citrate, Sucralose, Zinc Chloride

Questions? call (800) 473-1205

Formulated and Distribured by:

Prevention Health Sciences, Inc.

Raleigh, IL 62977

800-473-1205

PHS Brands

PACKAGE LABEL

ALCOHOL FREE

PREVENTION™ MOUTH RINSE

Formulated for MOUTH SORE RELIEF

Oral Wound Cleanser For Common Mouth Sores

- CANKER SORES
- IRRITATION FROM BRACES
- MINOR MOUTH INJURIES

Soothing Mint

NET. 16 FL OZ (1 PT) 473 ML